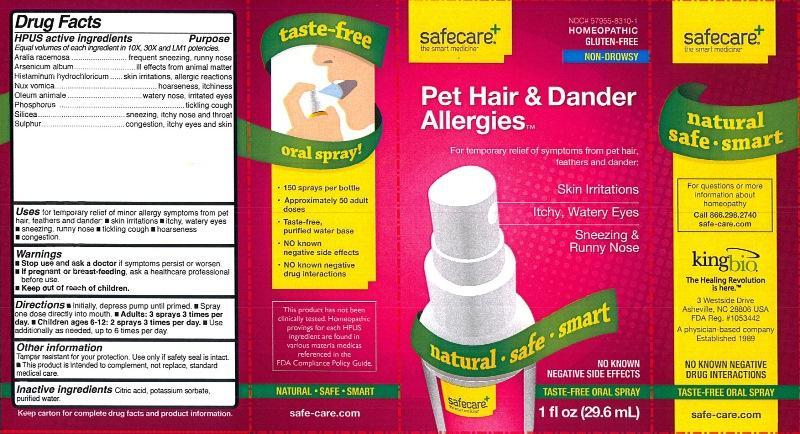 DRUG LABEL: Pet Hair and Dander Allergies
NDC: 57955-8310 | Form: LIQUID
Manufacturer: King Bio Inc.
Category: homeopathic | Type: HUMAN OTC DRUG LABEL
Date: 20131112

ACTIVE INGREDIENTS: ARALIA RACEMOSA ROOT 10 [hp_X]/29.6 mL; ARSENIC TRIOXIDE 10 [hp_X]/29.6 mL; HISTAMINE DIHYDROCHLORIDE 10 [hp_X]/29.6 mL; STRYCHNOS NUX-VOMICA SEED 10 [hp_X]/29.6 mL; CERVUS ELAPHUS HORN OIL 10 [hp_X]/29.6 mL; PHOSPHORUS 10 [hp_X]/29.6 mL; SILICON DIOXIDE 10 [hp_X]/29.6 mL; SULFUR 10 [hp_X]/29.6 mL
INACTIVE INGREDIENTS: CITRIC ACID MONOHYDRATE; POTASSIUM SORBATE; WATER

Pet Hair & Dander Allergies™

Drug Facts

____________________________________________________________________________________________________________

Equal volumes of each ingredient in 10X, 30X, and LM1 potencies.

HPUS active ingredients: Aralia racemosa, Arsenicum album, Histaminum hydrochloricum, Nux vomica, Oleum animale, Phosphorus, Silicea, Sulphur.

INDICATIONS AND USAGE

Uses for temporary relief of minor allergy symptoms from pet hair, feathers and dander: •skin irritations •itchy, watery eyes •sneezing, runny nose •tickling cough •hoarseness •congestion.

Warnings

- Stop use and ask a doctor if symptoms persist or worsen.
- If pregnant or breast-feeding, ask a healthcare professional before use.

- Keep out of reach of children.

Directions:

- Initially, depress pump until primed.
- Spray one dose directly into mouth.
- Adults: 3 sprays 3 times per day.
- Children ages 6-12: 2 sprays 3 times per day.
- Use additionally as needed, up to 6 times per day.

OTHER SAFETY INFORMATION

Tamper resistant for your protection. Use only if safety seal is intact.

- This product is intended to complement, not replace, standard medical care.

Inactive Ingredients: Citric acid, potassium sorbate, purified water.

Drug Facts

__________________________________________________________________________________________________________________

HPUS active ingredients Purpose

Equal volumes of each ingredient in 10X, 30X, and LM1 potencies.

Aralia racemosa.................................................................frequent sneezing, runny nose

Arsenicum album...............................................................ill effects from animal matter

Histaminum hydrochloricum................................................skin irritations, allergic reactions

Nux vomica.......................................................................hoarseness, itchiness

Oleum animale..................................................................watery nose, irritated eyes

Phosphorus.......................................................................tickling cough

Silicea..............................................................................sneezing, itchy nose and throat

Sulphur............................................................................congestion, itchy eyes and skin